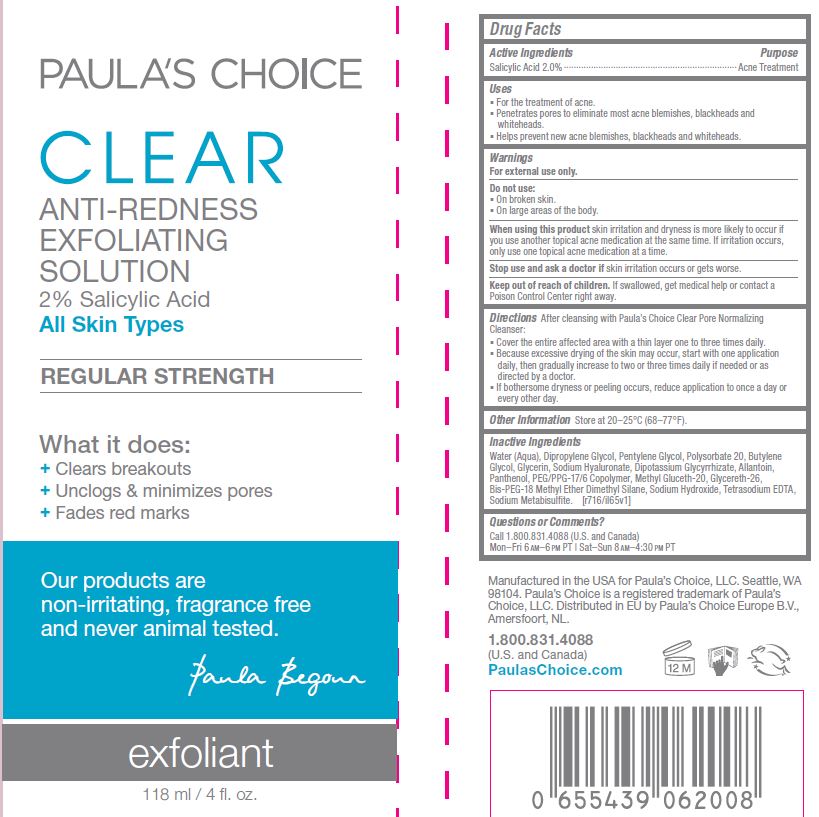 DRUG LABEL: Clear Exfoliating Solution
NDC: 56152-5002 | Form: CREAM
Manufacturer: Cosmetic Enterprises Ltd
Category: otc | Type: HUMAN OTC DRUG LABEL
Date: 20251010

ACTIVE INGREDIENTS: SALICYLIC ACID 2 g/100 mL
INACTIVE INGREDIENTS: WATER; DIPROPYLENE GLYCOL; PENTYLENE GLYCOL; POLYSORBATE 20; BUTYLENE GLYCOL; GLYCERIN; HYALURONATE SODIUM; GLYCYRRHIZINATE DIPOTASSIUM; ALLANTOIN; PANTHENOL; PEG/PPG-17/6 COPOLYMER; METHYL GLUCETH-20; GLYCERETH-26; BIS-PEG-18 METHYL ETHER DIMETHYL SILANE; SODIUM HYDROXIDE; EDETATE SODIUM; SODIUM METABISULFITE

Clear Exfoliating Solution

Active Ingredeints Purpose

Salicylic Acd 2.0% ................... Acne Treatment

Uses

- For the treatment of acne
- Penetrates Pores to eliminate most acne blemishes, blackheads, and whiteheads
- Helps prevent new acne blemishes, blackheads and whiteheads

KEEP OUT OF REACH OF CHILDREN

Keep out of the reach of children.If swallowed, get medical help or contact a Poison Control Center right away.

Stop use and ask a doctorif skin irritation occurs or gets worse

Warning

- For external use only
- When using this product skin irritation and dryness is more likely to occur if you use another topical acne medication at the same time. If irritation occurs, only use one topical acne medication at a time

DOSAGE AND ADMINISTRATION

DirectionsAfter cleansing with Paula's Choice Clear Pore Normalizing Cleanser

- Cover the entire affected area with a thin layer one to three times daily
- Because excessive drying out of the skin may occur, start with one application daily, then gradually increase to two or three times daily if needed or as directed by a doctor
- If bothersome dryness or peeling occurs, reduce application to once a day or every other day

INACTIVE INGREDIENT

Water (Aqua), Dipropylene Glycol, Pentylene Glycol, Polysorbate 20, Butylene Glycol, Glycerin, Sodium Hyaluronate, Dipotassium Glycrrhizate, Allantoin, Panthenol, PEG/PPG-17/6 Copolymer, Methyl Gluceth-20, Glycereth-26, Bis-PEG-18 Methyl Ether Dimethyl Silane, Sodium Hydroxide, Tetrasodium EDTA, Sodium Metabisulfite

PACKAGE LABEL

PAULA'S CHOICE

CLEAR

ANTI-REDNESS

EXFOLIATING SOLUTION

2% Salicylic Acid

All Skin Types

What it does:

- Clears breakouts
- Unclogs & Minimizes pores
- Fades red marks

118 ml / 4 fl. oz.